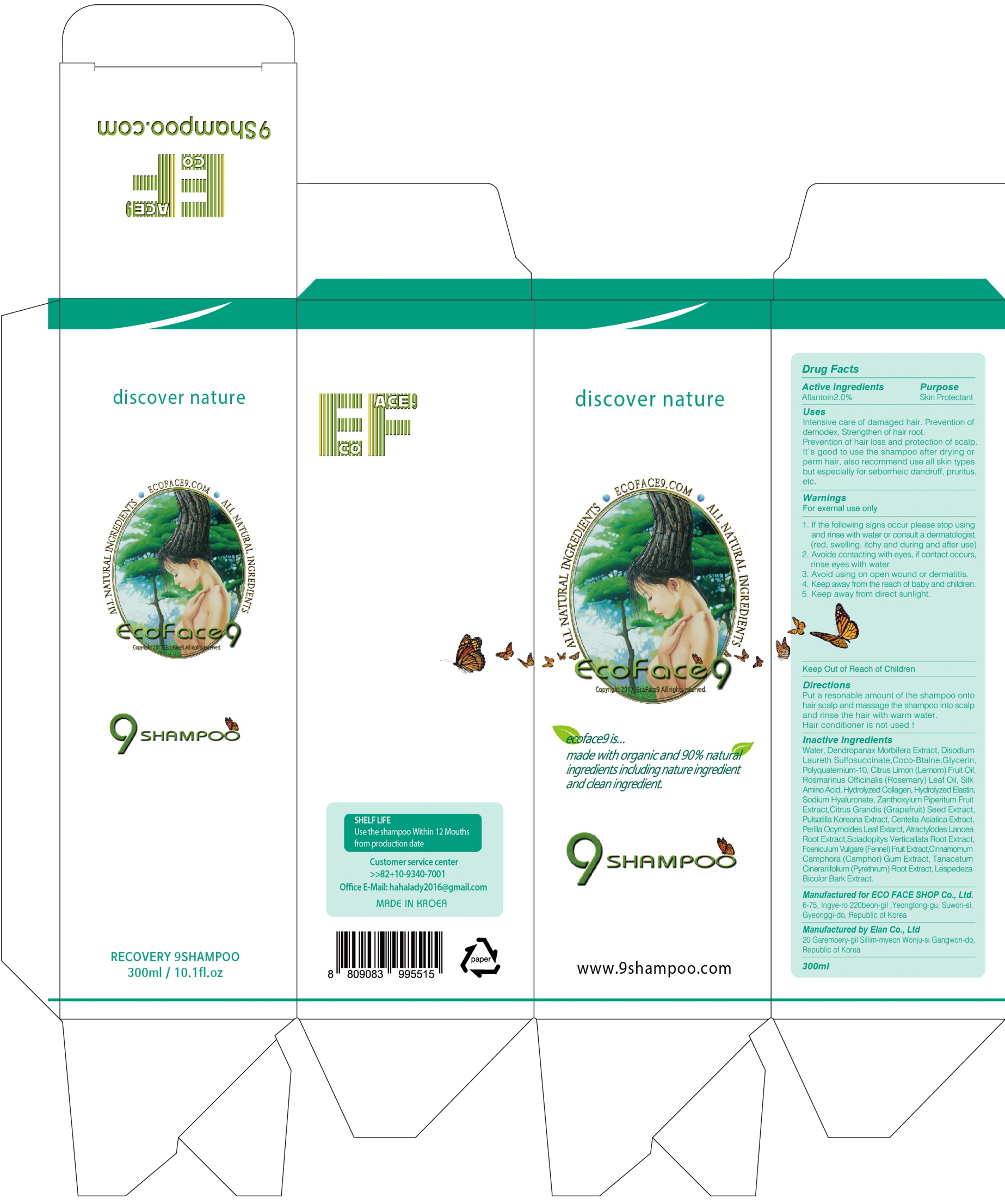 DRUG LABEL: ECO FACE 9
NDC: 71672-010 | Form: SHAMPOO
Manufacturer: Eco Face Shop
Category: otc | Type: HUMAN OTC DRUG LABEL
Date: 20170915

ACTIVE INGREDIENTS: Allantoin 6.0 g/300 mL
INACTIVE INGREDIENTS: Water; Glycerin

ACTIVE INGREDIENT

Active ingredients: Allantoin 2.0%

INACTIVE INGREDIENT

Inactive ingredients: Water,Dendropanax Morbifera Extract,Disodium Laureth Sulfosuccinate,Coco-Btaine,Glycerin,Polyquaternium-10,Citrus Limon (Lemom) Fruit Oil,Rosmarinus Officinalis (Rosemary) Leaf Oil,Silk Amino Acid,Hydrolyzed Collagen,Hydrolyzed Elastin, ,Zanthoxy Sodium Hyaluronate lum Piperitum Fruit Extract,Citrus Grandis (Grapefruit) Seed Extract,Pulsatilla Koreana Extract,Centella Asiatica Extract,Perilla Ocymoides Leaf Extarct,Atractylodes Lancea Root Extract,Sciadopitys Verticallata Root Extract,Foeniculum Vulgare (Fennel) Fruit Extract,Cinnamomum Camphora (Camphor) Gum Extract,Tanacetum Cinerariifolium (Pyrethrum) Root Extract,Lespedeza Bicolor Bark Extract.

PURPOSE

Purpose: Skin Protectant

WARNINGS

Warnings: For external use only 1.If the following signs occur ,please stop using and rinse with water or consult a dermatologist .(red, swelling,itchy and during and after use) 2.Avoide contacting with eyes,if contact occurs,rinse eyes with water. 3.Avoid using on open wound or dermatitis. 4.Keep away from the reach of baby and children. 5.Keep away from direct sunlight.

KEEP OUT OF REACH OF CHILDREN

Keep away from the reach of baby and children.

Uses

Uses: Intensive care of damaged hair.Prevention of demodex,Strengthen of hair root.Prevention of hair loss and protection of scalp.It's good to use the shampoo after drying or perm hair ,also recommend use all skin types but especially for seborrheic dermatitis,dandruff, pruritus,etc.

Directions

Directions: Put a resonable amount of the shmpoo onto hair scalp and massage the shampoo into scalp ,and rinse the hair with warm water. Hair conditioner is not used!